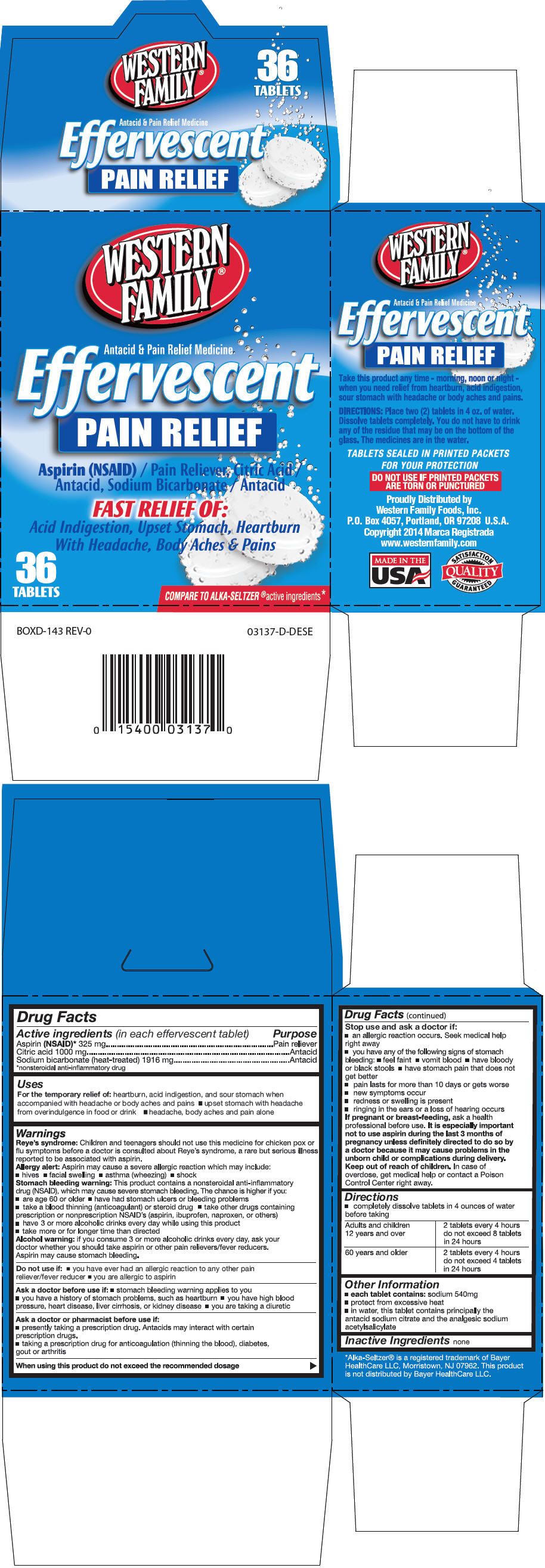 DRUG LABEL: Effervescent Pain Relief
NDC: 55312-469 | Form: TABLET, EFFERVESCENT
Manufacturer: Western Family Foods, Inc.
Category: otc | Type: HUMAN OTC DRUG LABEL
Date: 20141007

ACTIVE INGREDIENTS: Aspirin 325 mg/1 1; Citric Acid Monohydrate 1000 mg/1 1; Sodium Bicarbonate 1916 mg/1 1

Effervescent Pain Relief

Drug Facts

ACTIVE INGREDIENT

Active ingredients (in each effervescent tablet) | Purpose
Aspirin (NSAID) [nonsteroidal anti-inflammatory drug] 325 mg | Pain reliever
Citric acid 1000 mg | Antacid
Sodium bicarbonate (heat-treated) 1916 mg | Antacid

Uses

For the temporary relief of: heartburn, acid indigestion, and sour stomach when accompanied with headache or body aches and pains

- upset stomach with headache from overindulgence in food or drink
- headache, body aches and pain alone

Warnings

Reye's syndrome

Children and teenagers should not use this medicine for chicken pox or flu symptoms before a doctor is consulted about Reye's syndrome, a rare but serious illness reported to be associated with aspirin.

Allergy alert

Aspirin may cause a severe allergic reaction which may include:

- hives
- facial swelling
- asthma (wheezing)
- shock

Stomach bleeding warning

This product contains a nonsteroidal anti-inflammatory drug (NSAID), which may cause severe stomach bleeding. The chance is higher if you:

- are age 60 or older
- have had stomach ulcers or bleeding problems
- take a blood thinning (anticoagulant) or steroid drug
- take other drugs containing prescription or nonprescription NSAID's (aspirin, ibuprofen, naproxen, or others)
- have 3 or more alcoholic drinks every day while using this product
- take more or for longer time than directed

Alcohol warning: if you consume 3 or more alcoholic drinks every day, ask your doctor whether you should take aspirin or other pain relievers/fever reducers. Aspirin may cause stomach bleeding.

Do not use if

- you have ever had an allergic reaction to any other pain reliever/fever reducer
- you are allergic to aspirin

Ask a doctor before use if

- stomach bleeding warning applies to you
- you have a history of stomach problems, such as heartburn
- you have high blood pressure, heart disease, liver cirrhosis, or kidney disease
- you are taking a diuretic

Ask a doctor or pharmacist before use if

- presently taking a prescription drug. Antacids may interact with certain prescription drugs.
- taking a prescription drug for anticoagulation (thinning the blood), diabetes, gout or arthritis

When using this product do not exceed the recommended dosage

Stop use and ask a doctor if

- an allergic reaction occurs. Seek medical help right away
- you have any of the following signs of stomach bleeding:
  - feel faint
  - vomit blood
  - have bloody or black stools
  - have stomach pain that does not get better
- pain lasts for more than 10 days or gets worse
- new symptoms occur
- redness or swelling is present
- ringing in the ears or a loss of hearing occurs

PREGNANCY OR BREAST FEEDING

If pregnant or breast-feeding, ask a health professional before use. It is especially important not to use aspirin during the last 3 months of pregnancy unless definitely directed to do so by a doctor because it may cause problems in the unborn child or complications during delivery.

Keep out of reach of children. In case of overdose, get medical help or contact a Poison Control Center right away.

Directions

- completely dissolve tablets in 4 ounces of water before taking

Adults and children 12 years and over | 2 tablets every 4 hours do not exceed 8 tablets in 24 hours
60 years and older | 2 tablets every 4 hours do not exceed 4 tablets in 24 hours

Other Information

- each tablet contains: sodium 540 mg
- protect from excessive heat
- in water, this tablet contains principally the antacid sodium citrate and the analgesic sodium acetylsalicylate

Inactive Ingredients

none

Proudly Distributed by
Western Family Foods, Inc.
P.O. Box 4057, Portland, OR 97208 U.S.A.

PRINCIPAL DISPLAY PANEL - 36 Tablet Carton

WESTERN
FAMILY®

Antacid & Pain Relief Medicine
Effervescent
PAIN RELIEF

Aspirin (NSAID) / Pain Reliever, Citric Acid /
Antacid, Sodium Bicarbonate / Antacid

FAST RELIEF OF:

Acid Indigestion, Upset Stomach, Heartburn
With Headache, Body Aches & Pains

36
TABLETS

COMPARE TO ALKA-SELTZER®active ingredients*